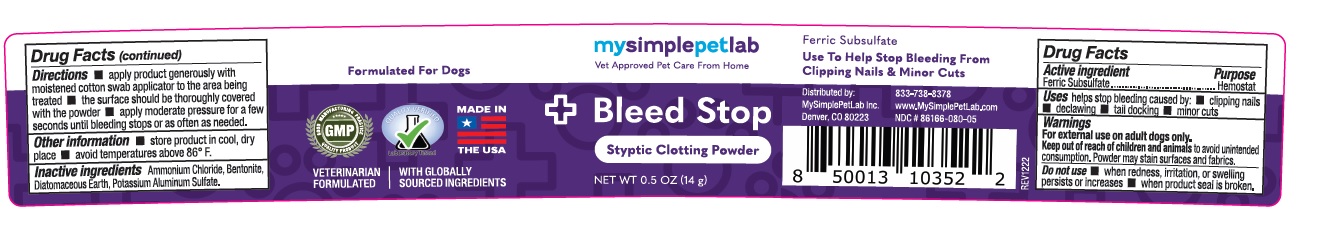 DRUG LABEL: MySimplePetLab Bleed Stop
NDC: 86166-080 | Form: POWDER
Manufacturer: Mysimplepetlab Inc
Category: animal | Type: OTC ANIMAL DRUG LABEL
Date: 20230316

ACTIVE INGREDIENTS: FERRIC SUBSULFATE 1 g/100 g
INACTIVE INGREDIENTS: AMMONIUM CHLORIDE; BENTONITE; DIATOMACEOUS EARTH; POTASSIUM; ALUMINUM SULFATE

mysimplepetlab Bleed Stop

Active ingredient

Ferric Subsulfate

Purpose

Hemostat

Uses

helps stop bleeding caused by: • clipping nails • declawing • tail docking • minor cuts

Warnings

For external use on adult dogs only.
Keep out of reach of children and animals to avoid unintended consumption. Powder may stain surfaces and fabrics.

Do not use • when redness, irritation, or swelling persists or increases • when product seal is broken.

Directions

• apply product generously with moistened cotton swab applicator to the area being treated • the surface should be thoroughly covered with the powder • apply moderate pressure for a few seconds until bleeding stops or as often as needed.

Other information

• store product in cool, dry place • avoid temperatures above 86° F.

Inactive ingredients

Ammonium Chloride, Bentonite, Diatomaceous Earth, Potassium Aluminum Sulfate.

Vet Approved Pet Care From Home

Styptic Clotting Powder

Formulated For Dogs

VETERINARIAN FORMULATED | WITH GLOBALLY SOURCED INGREDIENTS

MADE IN THE USA

Distributed by:
MySimplePetLab Inc.
Denver, CO 80223
833-738-8378
www.MySimplePetLab.com